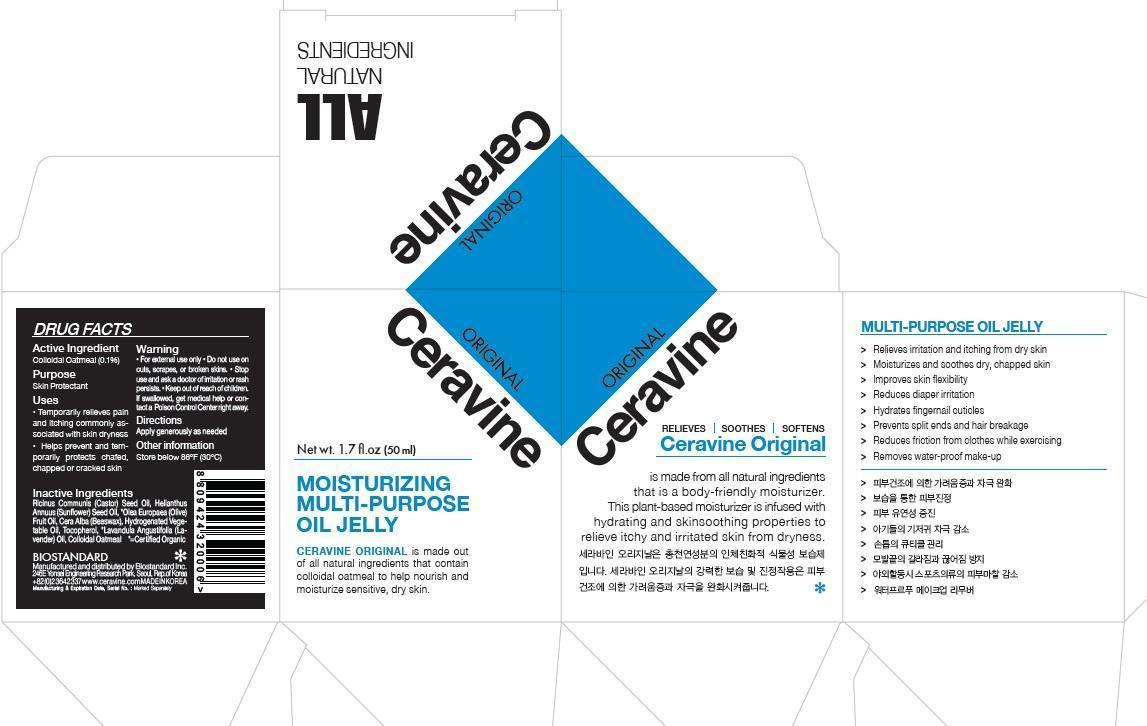 DRUG LABEL: Ceravine Original
NDC: 61403-020 | Form: JELLY
Manufacturer: Biostandard Inc.
Category: otc | Type: HUMAN OTC DRUG LABEL
Date: 20150724

ACTIVE INGREDIENTS: OATMEAL 0.0485 g/50 g
INACTIVE INGREDIENTS: YELLOW WAX; OLIVE OIL; TOCOPHEROL; SUNFLOWER OIL; LAVENDER OIL; CASTOR OIL

Drug Facts

Active ingredient

Colloidal Oatmeal (0.1%)

Purpose

Skin Protectant

Uses

- Temporarily relieves pain and itching commonly associated with skin dryness
- Helps prevent and temporarily protects chafed, chapped or cracked skin

Warnings

- For external use only

Do not use on

cuts, scrapes, or broken skins

Stop use and ask a doctor

if irritation or rash persists.

Keep out of reach of children.

If swallowed, get medical help or contact a Poison Control Center right away.

Directions

Apply generously as needed.

Other information

Store below 86 F (30 C)

Inactive ingredients

Ricinus Communis (Castor) Seed Oil, Helianthus Annus (Sunflower) Seed Oil, Olea Europaea (Olive) Fruit Oil, Cera Alba (Beeswax), Hydrogenated Vegetable Oil, Tocopherol, Lavandula Angustifolia (Lavender) Oil, Colloidal Oatmeal

Principal Display Panel

Ceravine ORIGINAL

ALL NATURAL INGREDIENTS

Net Wt. 1.7 Fl.oz (50 ml)

MOISTURIZING MULTI-PURPOSE OIL JELLY